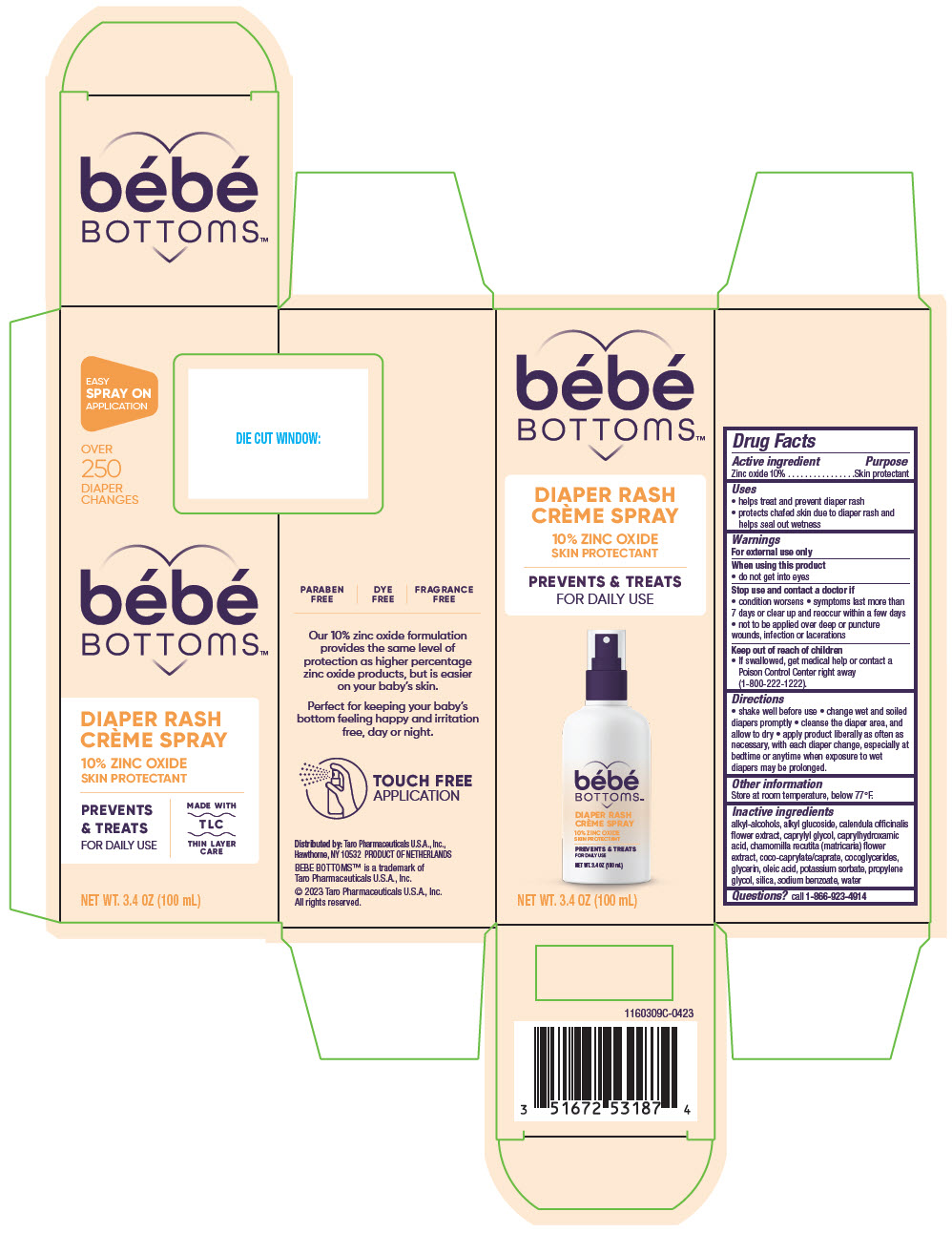 DRUG LABEL: Bebe Bottoms
NDC: 51672-5318 | Form: SPRAY
Manufacturer: TARO PHARMACEUTICALS U.S.A., INC.
Category: otc | Type: HUMAN OTC DRUG LABEL
Date: 20250121

ACTIVE INGREDIENTS: ZINC OXIDE 100 mg/1 mL
INACTIVE INGREDIENTS: C14-22 ALCOHOLS; C12-20 ALKYL GLUCOSIDE; CALENDULA OFFICINALIS FLOWER; CAPRYLYL GLYCOL; CAPRYLHYDROXAMIC ACID; CHAMOMILE; COCOYL CAPRYLOCAPRATE; COCO-GLYCERIDES; GLYCERIN; OLEIC ACID; POTASSIUM SORBATE; PROPYLENE GLYCOL; SILICON DIOXIDE; SODIUM BENZOATE; WATER

Bebe Bottoms™

Drug Facts

Active ingredient

Zinc oxide 10%

Purpose

Skin protectant

Uses

- helps treat and prevent diaper rash
- protects chafed skin due to diaper rash and helps seal out wetness

Warnings

For external use only

When using this product

- do not get into eyes

Stop use and contact a doctor if

- condition worsens
- symptoms last more than 7 days or clear up and reoccur within a few days
- not to be applied over deep or puncture wounds, infection or lacerations

Keep out of reach of children

- If swallowed, get medical help or contact a Poison Control Center right away (1-800-222-1222).

Directions

- shake well before use
- change wet and soiled diapers promptly
- cleanse the diaper area, and allow to dry
- apply product liberally as often as necessary, with each diaper change, especially at bedtime or anytime when exposure to wet diapers may be prolonged.

Other information

Store at room temperature, below 77°F.

Inactive ingredients

alkyl-alcohols, alkyl glucoside, calendula officinalis flower extract, caprylyl glycol, caprylhydroxamic acid, chamomilla recutita (matricaria) flower extract, coco-caprylate/caprate, cocoglycerides, glycerin, oleic acid, potassium sorbate, propylene glycol, silica, sodium benzoate, water

Questions?

call 1-866-923-4914

Distributed by:Taro Pharmaceuticals U.S.A., Inc.,
Hawthorne, NY 10532 PRODUCT OF NETHERLANDS

PRINCIPAL DISPLAY PANEL - 100 mL Bottle Carton

bébé
BOTTOMS™

DIAPER RASH
CRÈME SPRAY

10% ZINC OXIDE
SKIN PROTECTANT

PREVENTS & TREATS
FOR DAILY USE

NET WT. 3.4 OZ (100 mL)